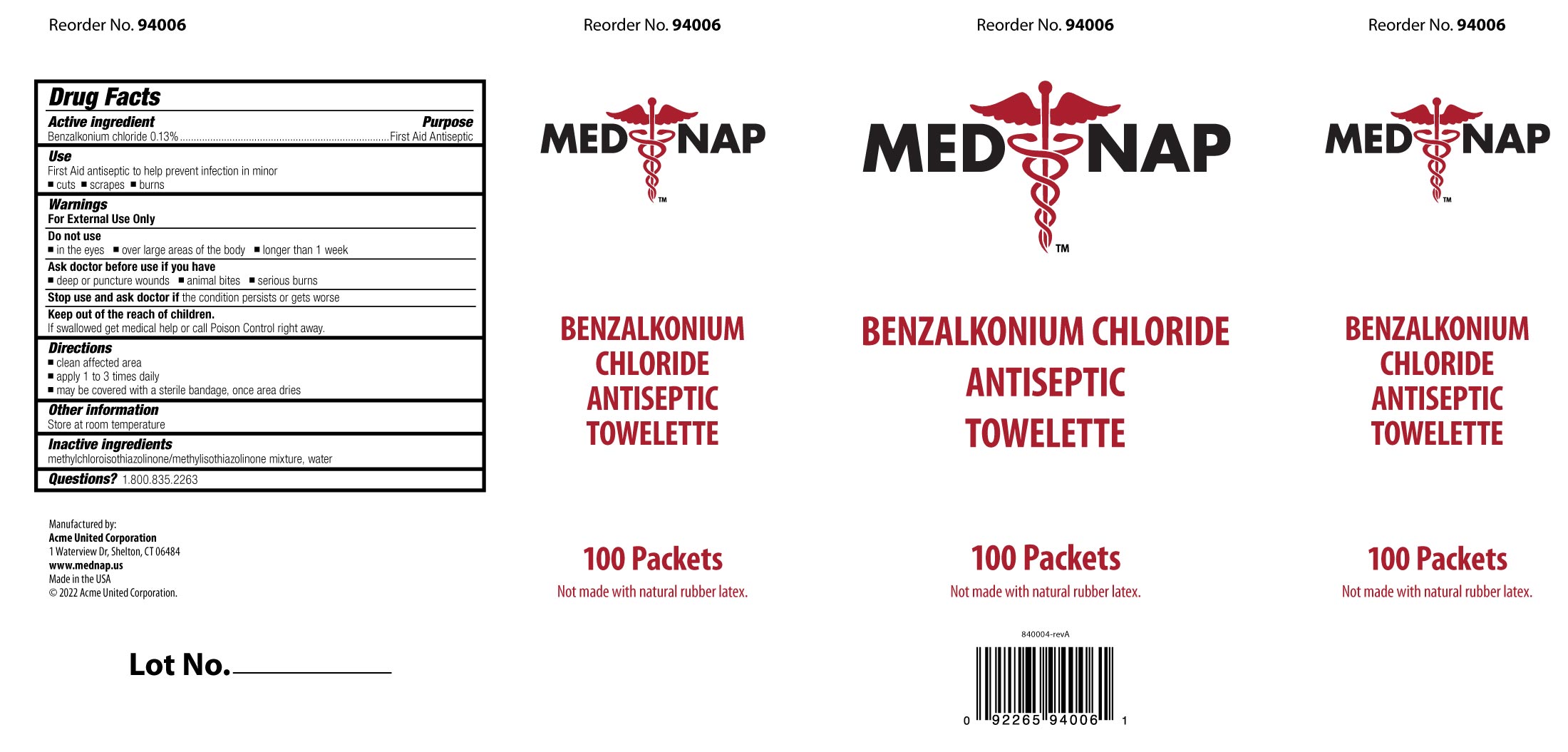 DRUG LABEL: MED NAP Benzalkonium Chloride Antiseptic
NDC: 0924-0246 | Form: LIQUID
Manufacturer: Acme United Corporation
Category: otc | Type: HUMAN OTC DRUG LABEL
Date: 20241109

ACTIVE INGREDIENTS: BENZALKONIUM CHLORIDE 0.0018 mg/1.35 mL
INACTIVE INGREDIENTS: WATER; METHYLCHLOROISOTHIAZOLINONE; METHYLISOTHIAZOLINONE

Med Nap Benzalkonium Chloride Antiseptic Towelette

Drug Facts Active Ingredient

Benzalkonium Chloride 0.13%

Purpose

First Aid Antiseptic

Uses

First Aid antiseptic to help prevent infection in minor

•cuts
•scrapes
•burns

Warnings

For External Use Only.

Do not use

•in the eyes
•over large areas of the body
•longer than 1 week

Ask a doctor before use if you have •Deep or puncture wounds •Animal bites •Serious burns

Stop use

Stop use and ask doctor if the condition persists or gets worse.

.

Keep out of reach of children.

If swallowed, get medical help or contact a Poison Control center right away.

Directions

To open: Tear packet open at notch, remove towelette, use it only once

•Clean affected area
•Apply 1 to 3 times daily
•May be covered with a sterile bandage, once area dries

Other Information

Store at room temperature

Inactive Ingredients

methylchloroisothiazolinone/methylisothiazolinone mixture, water

QUESTIONS

1.800.835.2263

Box Label